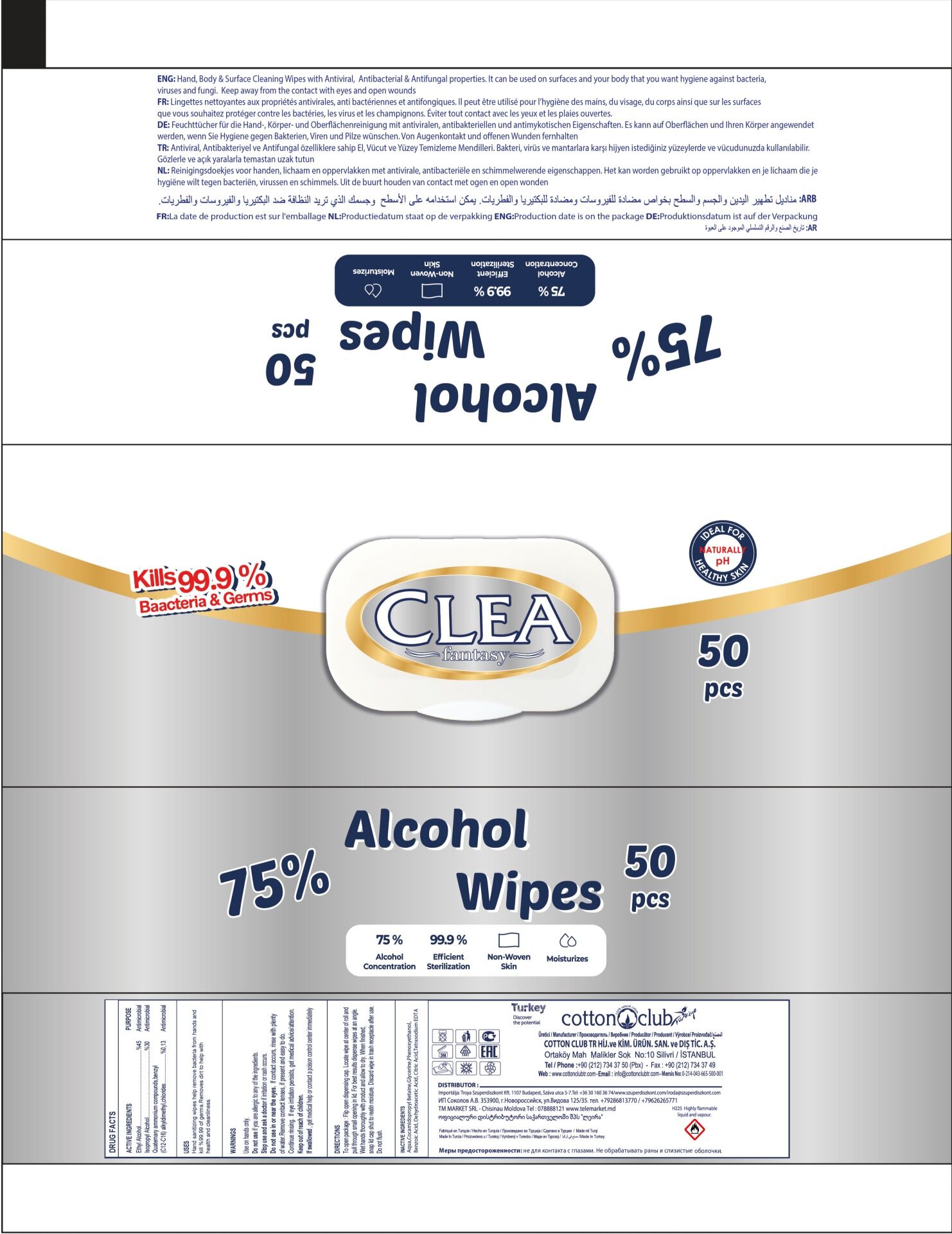 DRUG LABEL: Clea Fantasy Alcohol Wipes
NDC: 79585-050 | Form: SWAB
Manufacturer: COTTON CLUB TR HIJYENIK VE KIMYEVI ÜRÜNLER SAN.VE DIŞ TIC.AŞ.
Category: otc | Type: HUMAN OTC DRUG LABEL
Date: 20200703

ACTIVE INGREDIENTS: ALCOHOL 45 mL/75 mL; ISOPROPYL ALCOHOL 30 mL/75 mL
INACTIVE INGREDIENTS: WATER; COCAMIDOPROPYL BETAINE; GLYCERIN

OTC Active